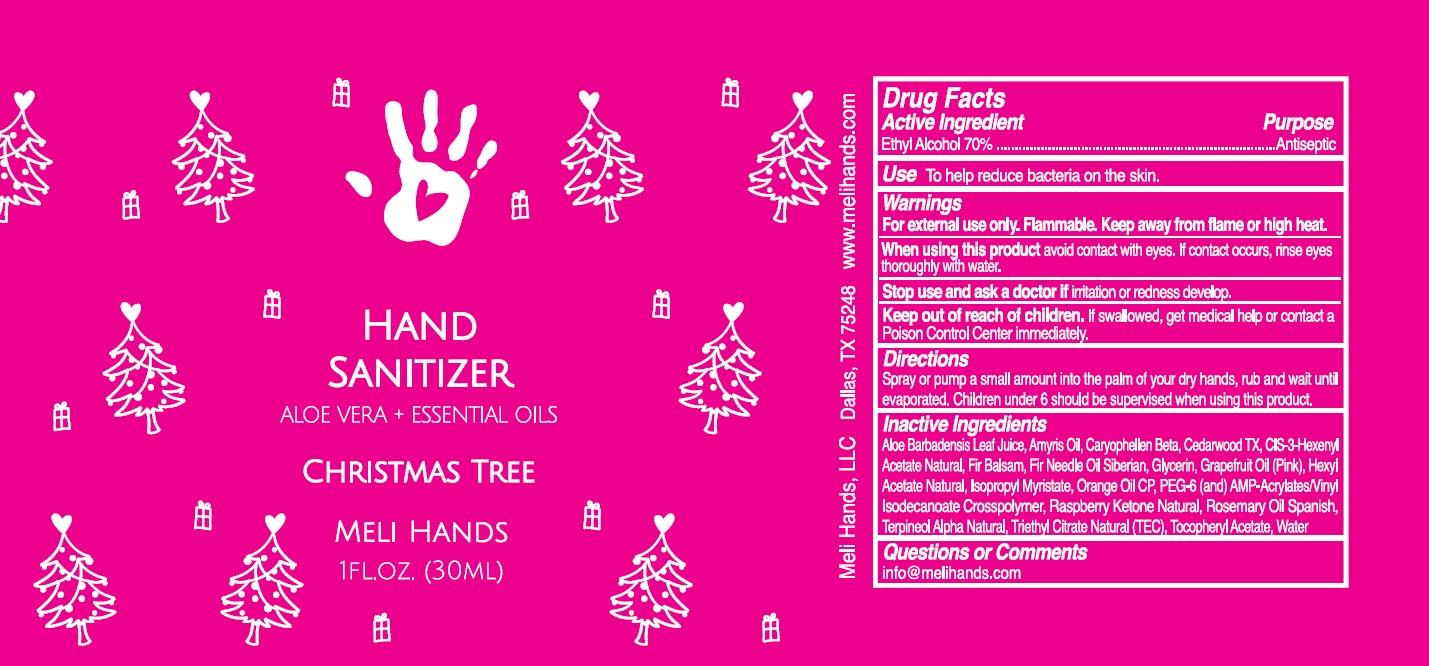 DRUG LABEL: MELI HANDS HAND SANITIZER
NDC: 79426-104 | Form: SPRAY
Manufacturer: MELI HANDS, LLC
Category: otc | Type: HUMAN OTC DRUG LABEL
Date: 20220914

ACTIVE INGREDIENTS: ALCOHOL 70 mL/100 mL
INACTIVE INGREDIENTS: ALOE VERA LEAF; AMYRIS BALSAMIFERA OIL; CARYOPHYLLENE; JUNIPERUS DEPPEANA WOOD OIL; 3-HEXENYL ACETATE, (3Z)-; CANADA BALSAM; ABIES SIBIRICA LEAF OIL; GLYCERIN; GRAPEFRUIT OIL; HEXYL ACETATE; ISOPROPYL MYRISTATE; ORANGE OIL; POLYETHYLENE GLYCOL 300; AMINOMETHYLPROPANOL; ACRYLATES/VINYL ISODECANOATE CROSSPOLYMER (10000 MPA.S NEUTRALIZED AT 0.5%); 4-(P-HYDROXYPHENYL)-2-BUTANONE; ROSEMARY OIL; TERPINEOL; TRIETHYL CITRATE; .ALPHA.-TOCOPHEROL ACETATE; WATER

MELI HANDS HAND SANITIZER

Active Ingredient

Ethyl Alcohol 70%

Purpose

Antiseptic

Use

To help reduce bacteria on the skin.

Warnings

For external use only. Flammable. Keep away from flame or high heat.

When using this product avoid contact with eyes. If contact occurs, rinse eyes thoroughly with water.

Stop use and ask a doctor if irritation or redness develop.

Keep out of reach of children. If swallowed, get medical help or contact a Poison Control Center immediately.

Directions

Spray or pump a small amount into the palm of your dry hands, rub and wait until evaporated. Children under 6 should be supervised when using this product.

Inactive Ingredients

Aloe Barbadensis Leaf Juice, Amyris Oil, Caryophellen Beta, Cedarwood TX, CIS-3-Hexenyl Acetate Natural, Fir Balsam, Fir Needle Oil Siberian, Glycerin, Grapefruit Oil (Pink), Hexyl Acetate Natural, Isopropyl Myristate, Orange Oil CP, PEG-6(and) AMP-Acrylates/Vinyl Isodecanoate Crosspolymer, Raspberry Ketone Natural, Rosemary Oil Spanish, Terpineol Alpha Natural, Triethyl Citrate Natural(TEC), Tocopheryl Acetate, Water

Questions or Comments

info@melihands.com

ALOE VERA + ESSENTIAL OILS

CHRISTMAS TREE

Meli Hands, LLC Dallas, TX 75248 www.melihands.com